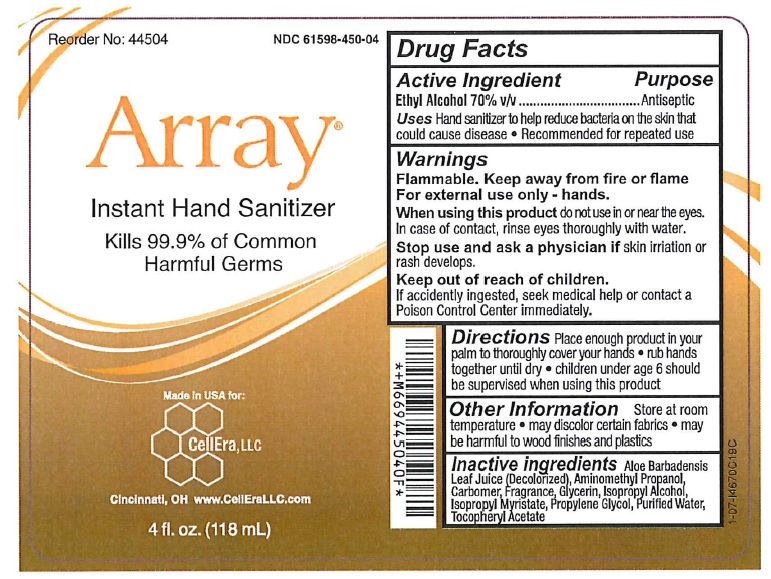 DRUG LABEL: Instant Hand Sanitizer
NDC: 61598-450 | Form: GEL
Manufacturer: LTC Products Inc.
Category: otc | Type: HUMAN OTC DRUG LABEL
Date: 20260112

ACTIVE INGREDIENTS: ALCOHOL 70 mL/100 mL
INACTIVE INGREDIENTS: CARBOMER 980; GLYCERIN; ISOPROPYL ALCOHOL; ISOPROPYL MYRISTATE; PROPYLENE GLYCOL; WATER; ALPHA-TOCOPHEROL ACETATE; ALOE VERA LEAF; AMINOMETHYLPROPANOL

INSTANT
HAND
SANITIZER

Drug Facts

Active ingredient

Ethyl Alcohol 70% v/v

Purpose

Antiseptic

Purpose

Antiseptic

Warnings

Flammable. Keep away from fire or flame

For external use only - hands.

WHEN USING

When using this productdo not use in or near the eyes. In case of contact, rinse eyes thoroughly with water.

Stop use and ask a physician ifskin irritation or rash develops.

Keep out of reach of children.If accidently ingested, seek medical help or contact a Poison Control Center immediately.

Directions

- place enough product in your palm to thoroughly cover your hands
- rub hands together briskly until dry
- children under 6 years of age should be supervised when using this product

Other Information

- store at normal room temperature
- may discolor certain fabrics
- may be harmful to wood finishes and plastics

Inactive ingredients

carbomer, fragrance, glycerin, isopropyl alcohol, isopropyl myristate, propylene glycol, purified water, tocopheryl acetate, aloe vera gel, AMP-95

PRINCIPAL DISPLAY PANEL

Reorder No: 44504 NDC 61596-450-04

Array

INSTANT

HAND
SANITIZER

KILLS 99.9%

Of Common Harmful Germs

Made in USA for:

CellEra, LLC

Cincinati, OH www.CellEraLLC.com

4 fl. oz. (118 mL)